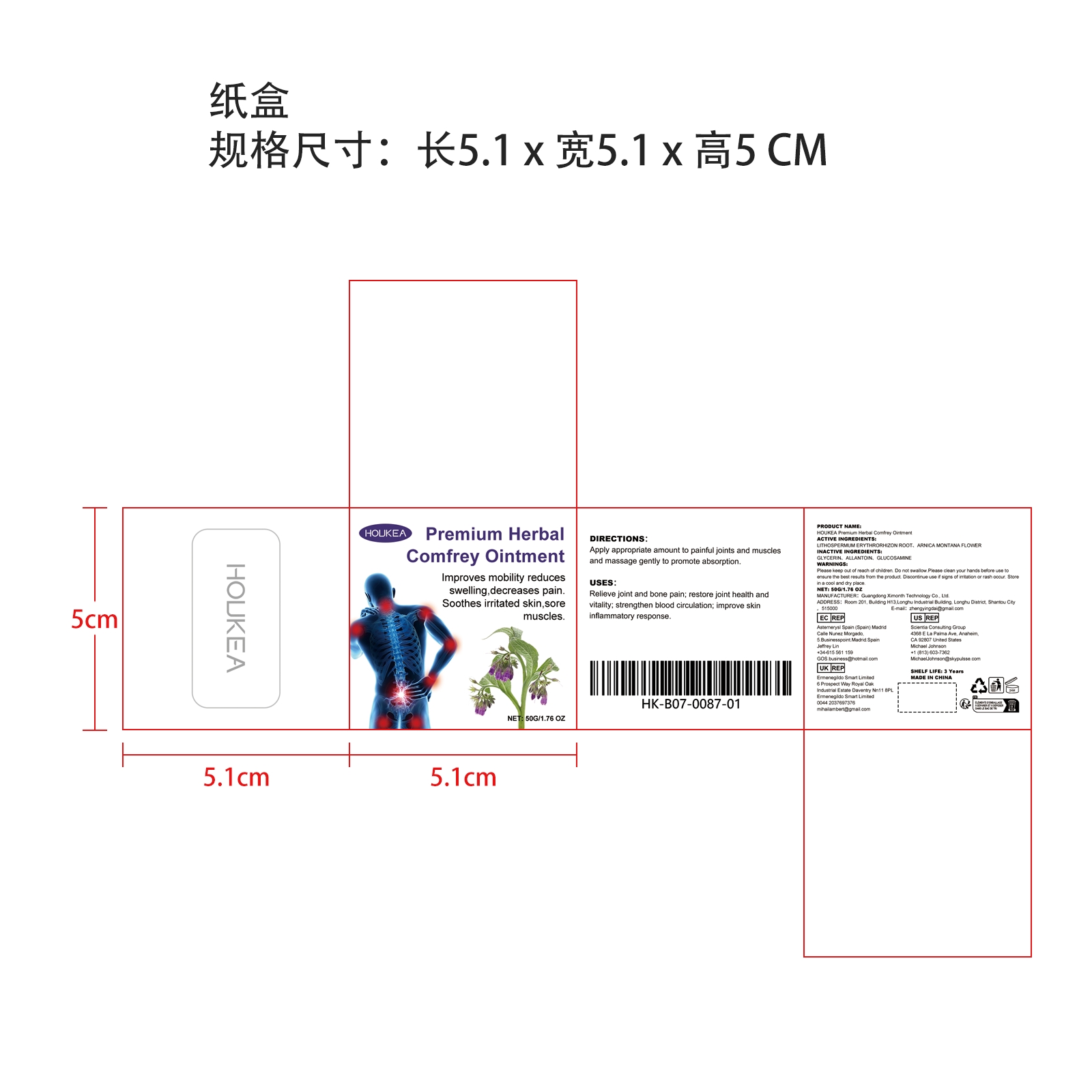 DRUG LABEL: HOUKEA Premium Herbal Comfrey
NDC: 84660-092 | Form: CREAM
Manufacturer: Guangdong Ximonth Technology Co., Ltd.
Category: otc | Type: HUMAN OTC DRUG LABEL
Date: 20241029

ACTIVE INGREDIENTS: ARNICA MONTANA FLOWER 5 g/50 g; LITHOSPERMUM ERYTHRORHIZON ROOT 15 g/50 g
INACTIVE INGREDIENTS: GLUCOSAMINE 15 g/50 g; GLYCERIN 7.5 g/50 g; ALLANTOIN 7.5 g/50 g

ACTIVE INGREDIENTS

LITHOSPERMUM ERYTHRORHIZON ROOT,ARNICA MONTANA FLOWER

PURPOSE

Relieve joint and bone pain; restore joint health and vitality; strengthen blood circulation; improve skin inflammatory response.

USES

Apply appropriate amount to painful joints and muscles and massage gently to promote absorption.

WARNINGS

Please keep out of reach of children. Do not swallow.Please clean your hands before use to ensure the best results from the product. Discontinue use if signs of irritation or rash occur. Store in a cool and dry place.

STOP USE

Discontinue use if signs of irritation or rash occur.

DO NOT USE

Discontinue use if signs of irritation or rash occur.

KEEP OUT OF REACH OF CHILDREN

Please keep out of reach of children. Do not swallow.

STORAGE AND HANDLING

Store in a cool and dry place.

INACTIVE INGREDIENT

GLYCERIN、ALLANTOIN、GLUCOSAMINE